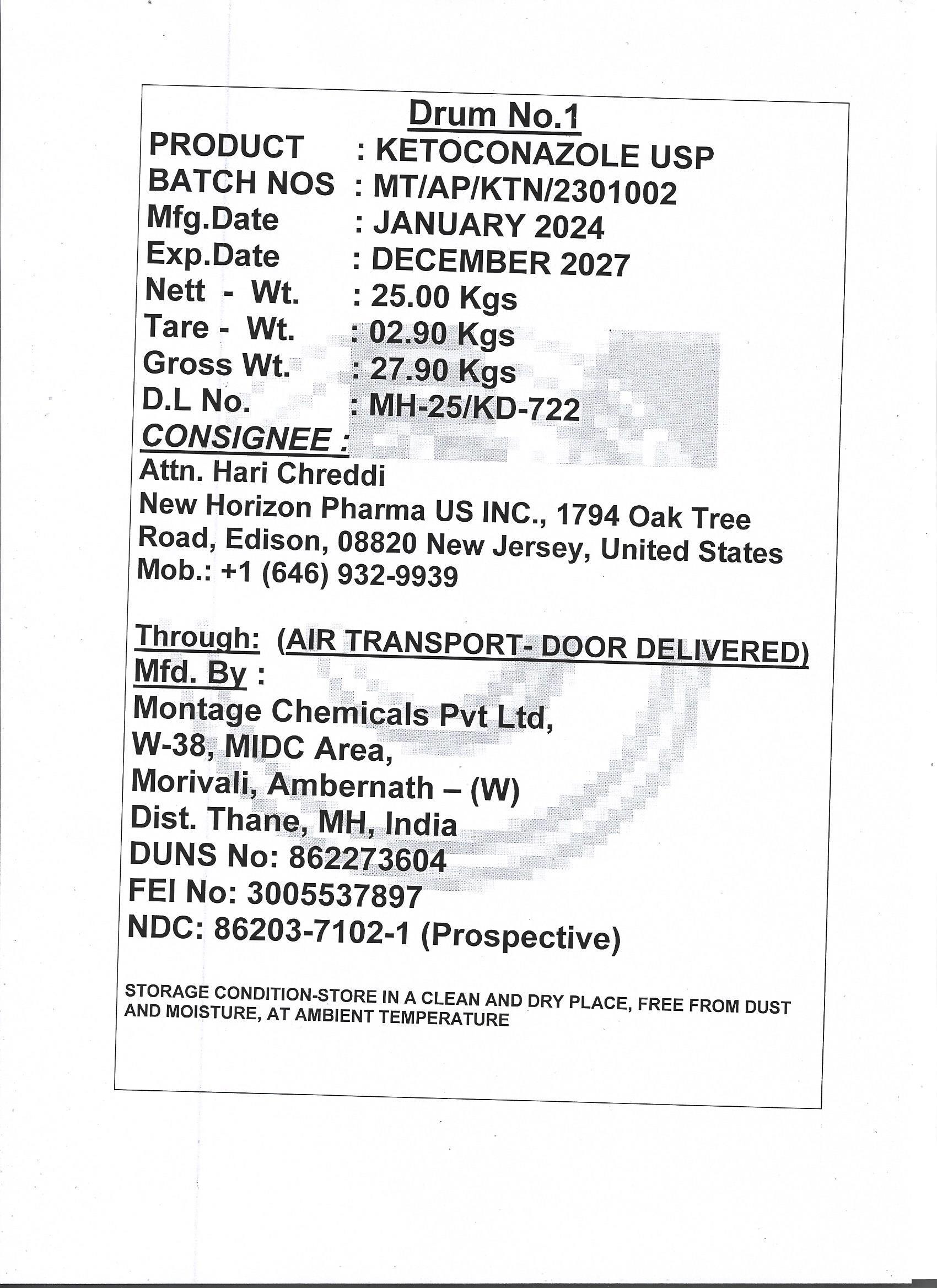 DRUG LABEL: KETOCONAZOLE
NDC: 86203-7102 | Form: POWDER
Manufacturer: MONTAGE CHEMICALS PRIVATE LIMITED
Category: other | Type: BULK INGREDIENT - ANIMAL DRUG
Date: 20240511

ACTIVE INGREDIENTS: KETOCONAZOLE 25 kg/25 kg

KETOCONAZOLE USP

PACKAGE LABEL

Drum No.1

PRODUCT : KETOCONAZOLE USP
BATCH NOS : MT/AP/KTN/2301002
Mfg.Date : JANUARY 2024
Exp.Date : DECEMBER 2027
Nett - Wt. : 25.00 Kgs
Tare - Wt. : 02.90 Kgs
Gross Wt. : 27.90 Kgs
D.L No. : MH-25/KD-722
CONSIGNEE :
Attn. Hari Chreddi
New Horizon Pharma US INC., 1794 Oak Tree
Road, Edison, 08820 New Jersey, United States
Mob.: +1 (646) 932-9939
Through: (AIR TRANSPORT- DOOR DELIVERED)
Mfd. By :
Montage Chemicals Pvt Ltd,
W-38, MIDC Area,
Morivali, Ambernath – (W)
Dist. Thane, MH, India
DUNS No: 862273604
FEI No: 3005537897
NDC: 86203-7102-1 (Prospective)

STORAGE CONDITION-STORE IN A CLEAN AND DRY PLACE, FREE FROM DUST
AND MOISTURE, AT AMBIENT TEMPERATURE

Add image transcription here...